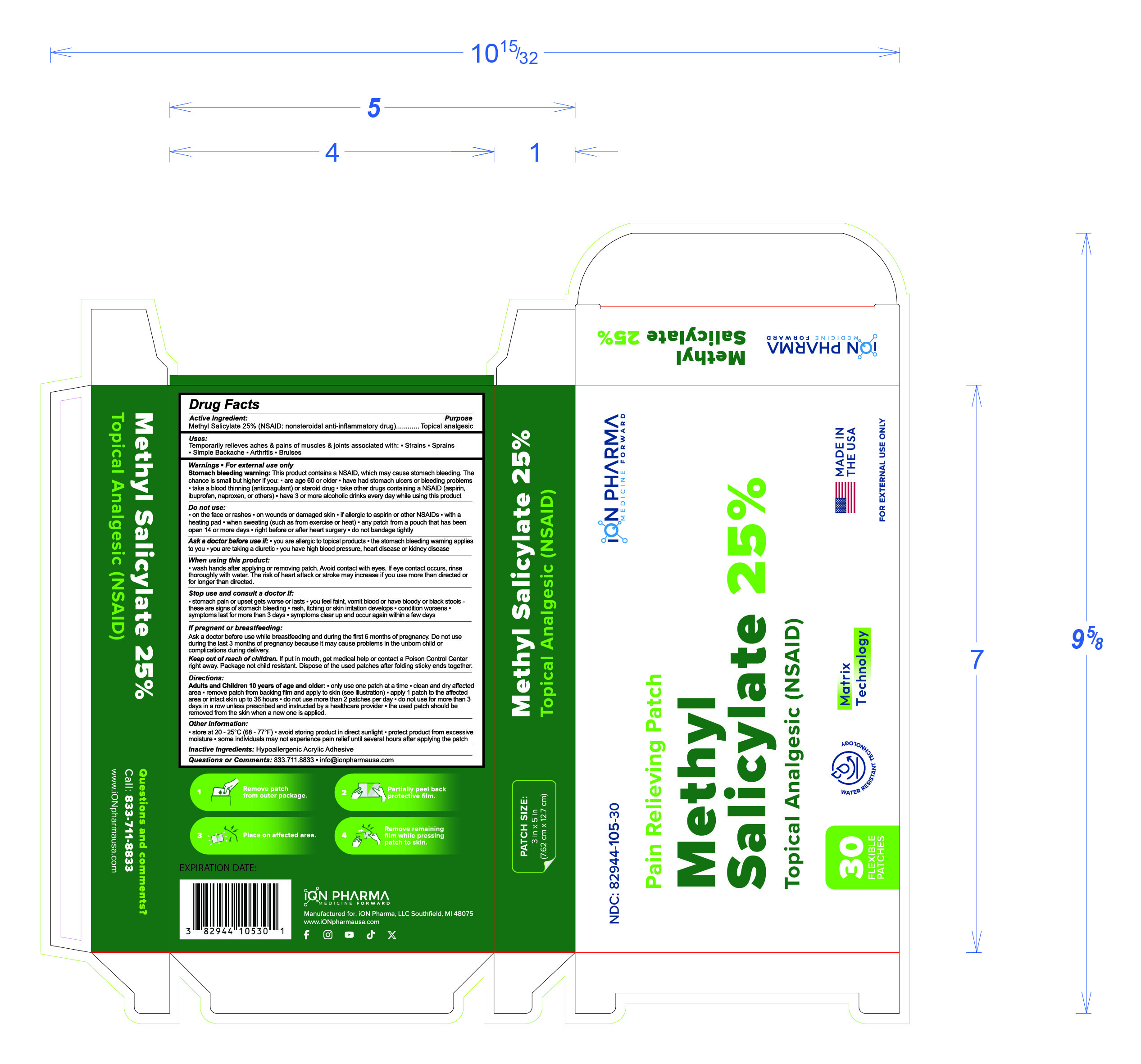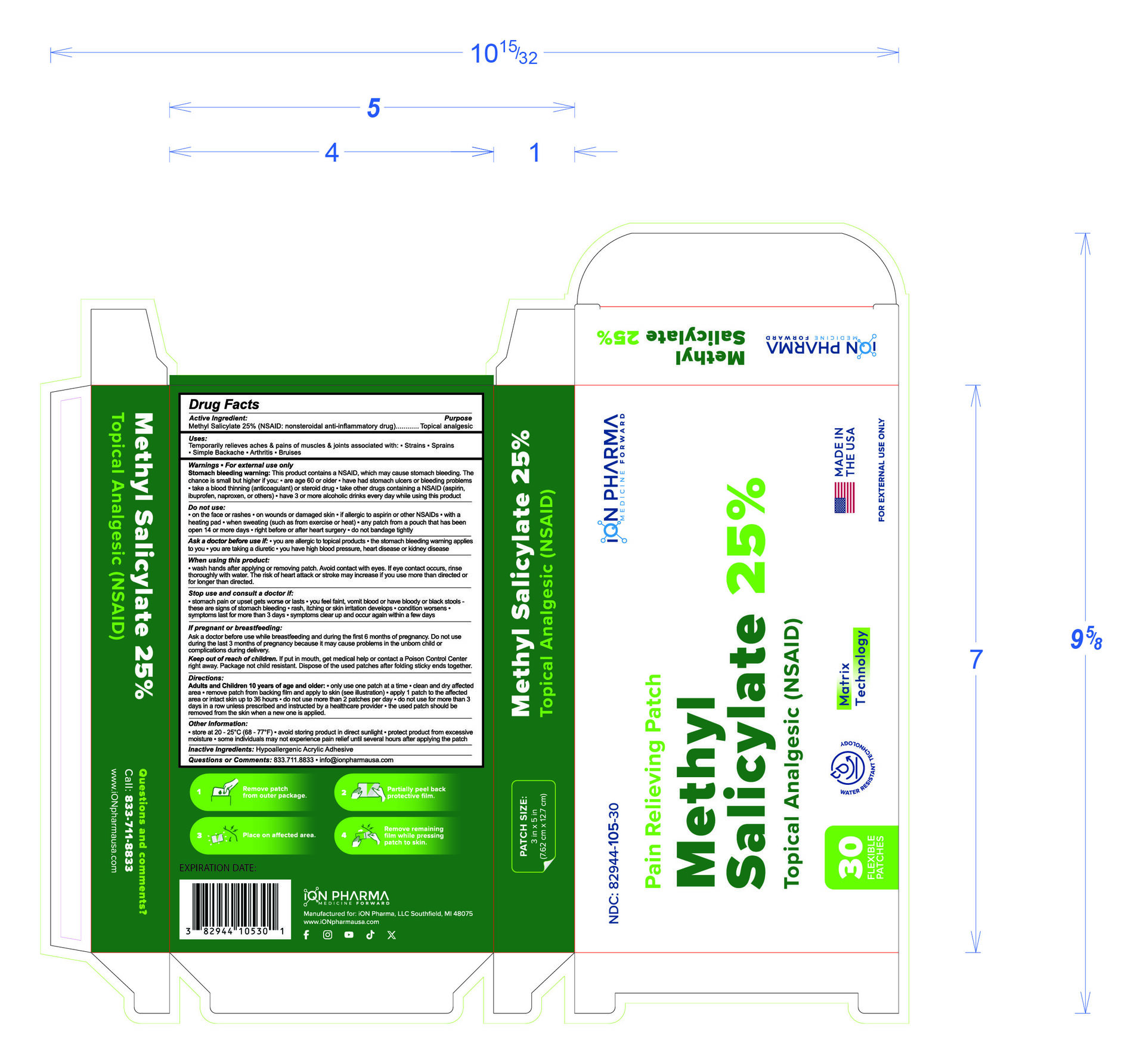 DRUG LABEL: Methyl Salicylate 25%
NDC: 82944-105 | Form: PATCH
Manufacturer: iON Pharma, LLC
Category: otc | Type: HUMAN OTC DRUG LABEL
Date: 20250718

ACTIVE INGREDIENTS: METHYL SALICYLATE 25 g/1 1
INACTIVE INGREDIENTS: ACRYLIC ACID

Methyl Salicylate 25%

Drug Facts section

Drug Facts

Active Ingredient: Purpose

Methyl Salicylate 25% (NSAID: nonsteroidal anti-inflammatory drug).......... Topical analgesic

Uses

Temporarily relieves aches & pains of muscles & joints associated with:

- Strains
- Sprains
- Simple Backache
- Arthritis
- Bruises

Do not use section

Warning: For external use only.

Stomach bleeding warning: This product contains a NSAID, which may cause stomach bleeding. The chance is small but higher if you:

- are age 60 or older have had stomach ulcers or bleeding problems
- take a blood thinning (anticoagulant) or steroid drug
- take other drugs containing a NSAID (aspirin, ibuprofen, naproxen, or others)
- have 3 or more alcoholic drinks every day while using this product

Do not use:

- on the face or rashes
- on wounds or damaged skin
- if allergic to aspirin or other NSAIDs
- with a heating pad when sweating (such as from exercise or heat)
- any patch from a pouch that has been open 14 or more days
- right before or after heart surgery
- do not bandage tightly

When using this product section

When using this product:

wash hands after applying or removing patch. Avoid contact with eyes. If eye contact occurs, rinse thoroughly with water. The risk of heart attack or stroke may increase if you use more than directed or for longer than directed.

Stop use section

Stop use and consult a doctor if:

- stomach pain or upset gets worse or lasts
- you feel faint, vomit blood or have bloody or black stools -these are signs of stomach bleeding
- rash, itching or skin irritation develops
- condition worsens
- symptoms last for more than 3 days symptoms clear up and occur again within a few days

If pregnant or breastfeeding section

If pregnant or breastfeeding:

Ask a doctor before use while breastfeeding and during the first 6 months of pregnancy. Do not use during the last 3 months of pregnancy because it may cause problems in the unbom child or complications during delivery.

Keep out of reach of children section

Keep out of reach of children. If put in mouth, get medical help or contact a Poison Control Center right away. Package not child resistant. Dispose of the used patches after folding sticky ends together.

Directions section

Directions:

Adults and Children 10 years of age and older:

- only use one patch at a time clean and dry affected
- area remove patch from backing film and apply to skin (see illustration)
- apply 1 patch to the affected area or intact skin up to 36 hours
- do not use more than 2 patches per day
- do not use for more than 3 days in a row unless prescribed and instructed by a healthcare provider
- the used patch should be removed from the skin when a new one is applied.

Storage and other information section

Other Information:

- store at 20-25°C (68-77°F)
- avoid storing product in direct sunlight
- protect product from excessive moisture
- some individuals may not experience pain relief until several hours after applying the patch

INACTIVE INGREDIENT

Hypoallergenic Acrylic Adhesive

Questions or comments section

Questions or Comments: 833.711.8833 info@ionpharmausa.com